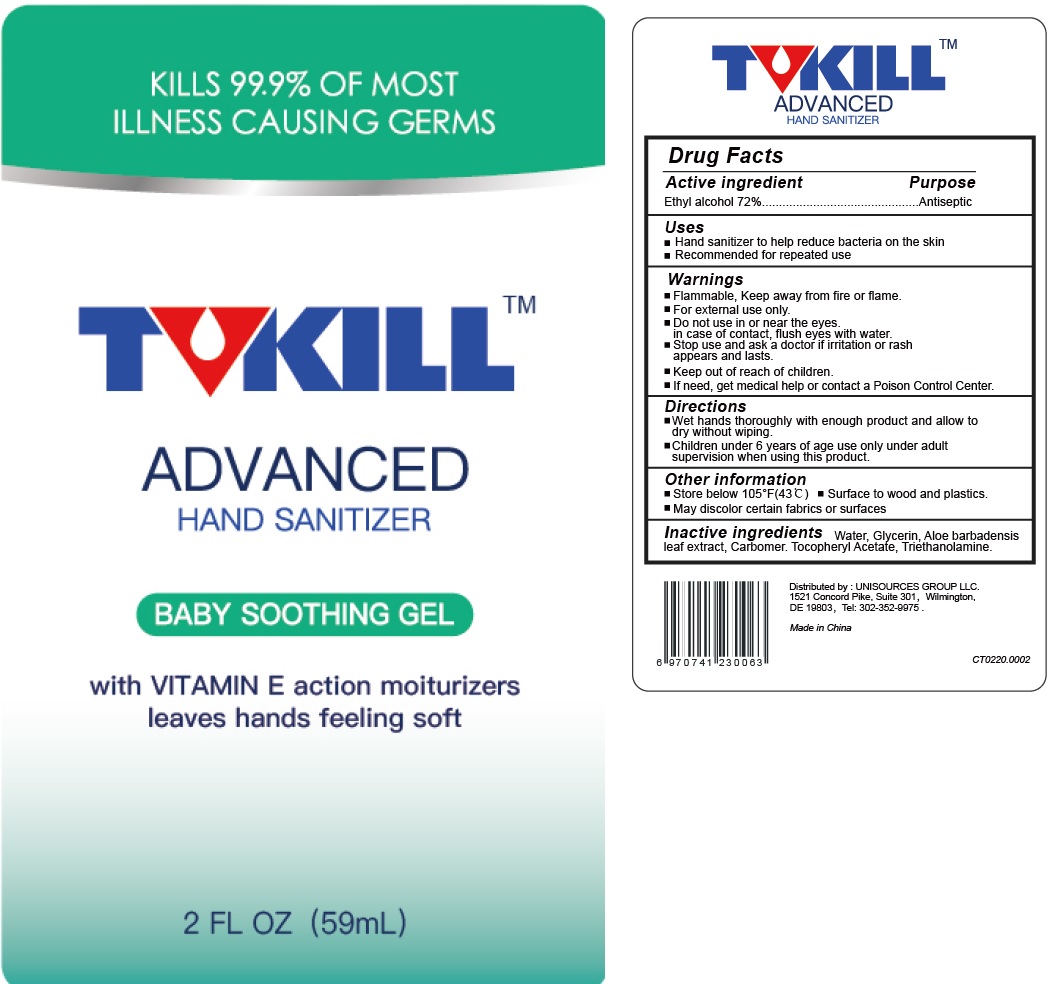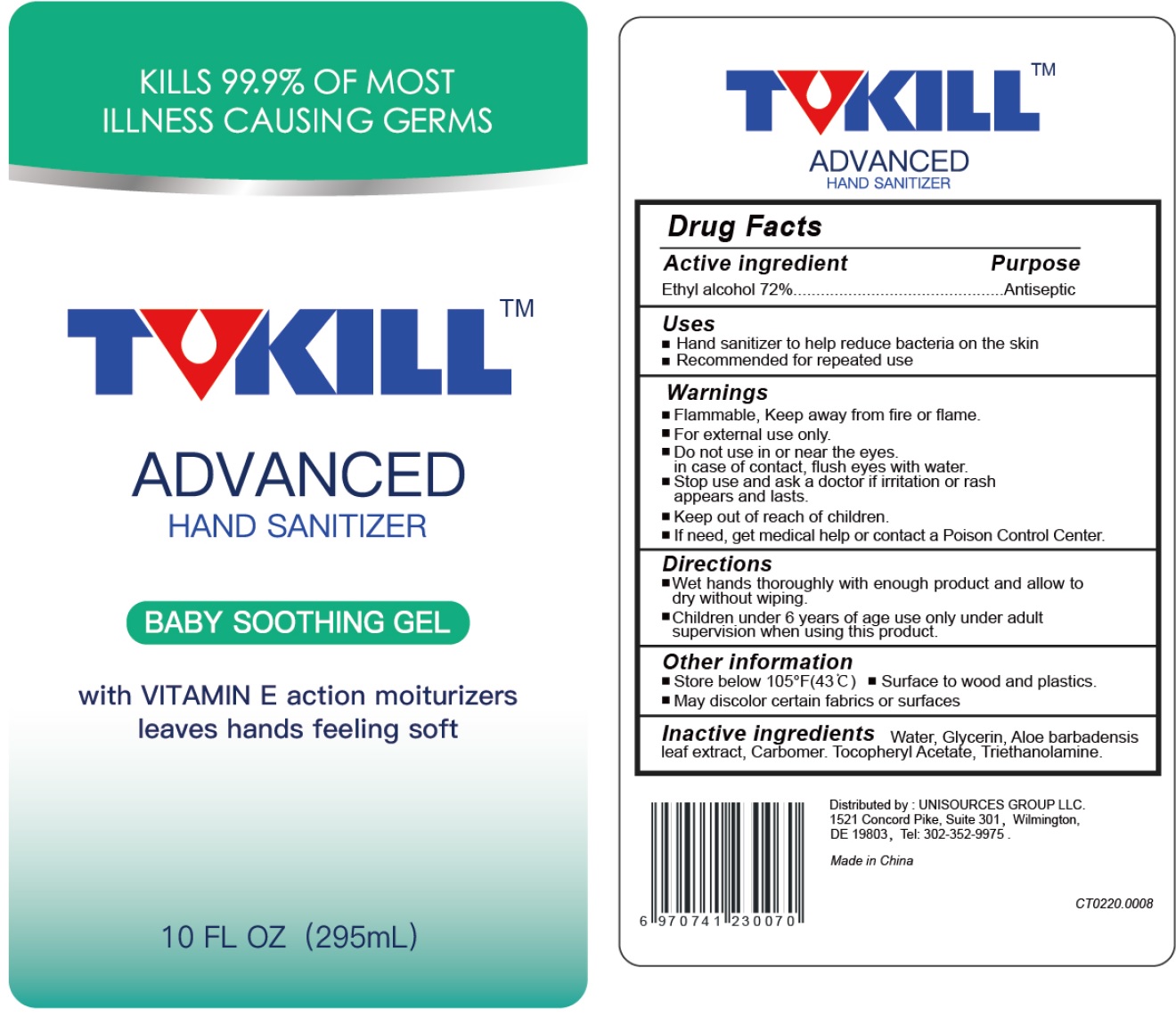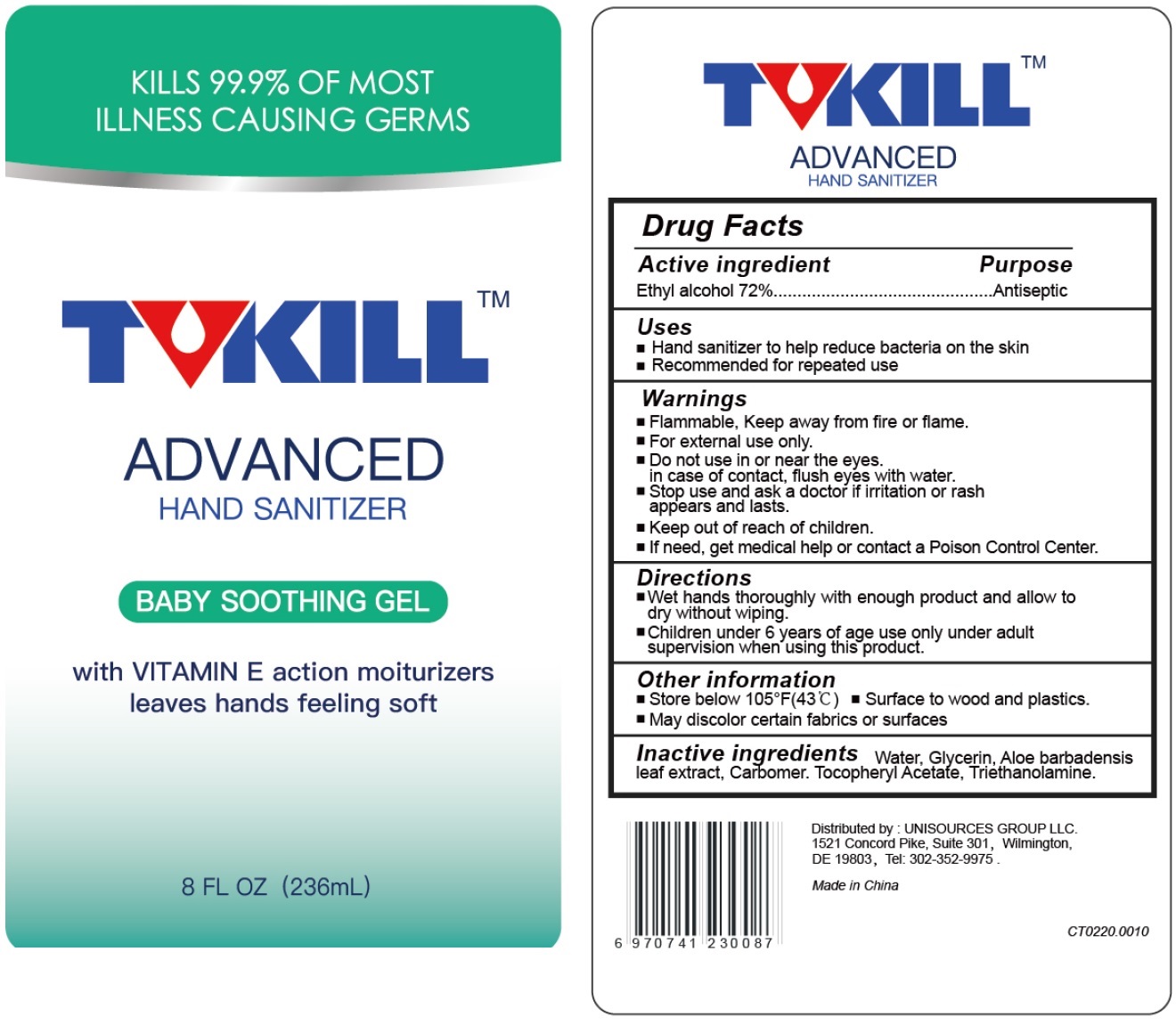 DRUG LABEL: Advanced Hand Sanitizer
NDC: 75311-000 | Form: GEL
Manufacturer: UNISOURCES GROUP LLC
Category: otc | Type: HUMAN OTC DRUG LABEL
Date: 20200624

ACTIVE INGREDIENTS: ALCOHOL 0.72 mL/1 mL
INACTIVE INGREDIENTS: WATER; GLYCERIN; ALOE VERA LEAF; CARBOMER HOMOPOLYMER, UNSPECIFIED TYPE; .ALPHA.-TOCOPHEROL ACETATE; TROLAMINE

Advanced Hand Sanitizer

Active ingredient

Ethyl alcohol 72%

Purpose

Antiseptic

Uses

- Hand sanitizer to help reduce bacteria on the skin
- Recommended for repeated use

Warnings

- Flammable, Keep away from fire or flame.
- For external use only.

Do not use

- in or near the eyes. in case of contact, flush eyes with water.

Stop use and ask a doctor if

- irritation or rash appears and lasts.

Keep out of reach of children.

- If need, get medical help or contact a Poison Control Center.

Directions

- Wet hands thoroughly with enough product and allow to dry without wiping.
- Children under 6 years of age use only under adult supervision when using this product.

Other information

- Store below 105°F(43 C)
- Surface to wood and plastics.
- May discolor certain fabrics or surfaces

Inactive ingredients

Water, Glycerin, Aloe barbadensis leaf extract, Carbomer, Tocopheryl Acetate, Triethanolamine.